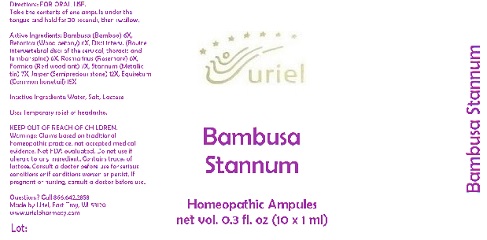 DRUG LABEL: Bambusa Stannum
NDC: 48951-2018 | Form: LIQUID
Manufacturer: Uriel Pharmacy Inc.
Category: homeopathic | Type: HUMAN OTC DRUG LABEL
Date: 20180518

ACTIVE INGREDIENTS: BAMBUSA VULGARIS WHOLE 6 [hp_X]/1 mL; STACHYS OFFICINALIS 6 [hp_X]/1 mL; BOS TAURUS INTERVERTEBRAL DISC 6 [hp_X]/1 mL; ROSMARINUS OFFICINALIS FLOWERING TOP 6 [hp_X]/1 mL; FORMICA RUFA 7 [hp_X]/1 mL; TIN 7 [hp_X]/1 mL; SILICON DIOXIDE 12 [hp_X]/1 mL; EQUISETUM ARVENSE TOP 15 [hp_X]/1 mL
INACTIVE INGREDIENTS: WATER; SODIUM CHLORIDE; LACTOSE

Bambusa Stannum

INDICATIONS AND USAGE

Directions: FOR ORAL USE.

DOSAGE AND ADMINISTRATION

Take the contents of one ampule under the tongue and hold for 30 seconds, then swallow.

ACTIVE INGREDIENT

Active Ingredients: Bambusa (Bamboo) 6X, Betonica (Wood betony) 6X, Disci interv. (Bovine intervertebral discs of the cervical, thoracic and lumbar spine) 6X, Rosmarinus (Rosemary) 6X, Formica (Red wood ant) 7X, Stannum (Metallic tin) 7X, Jasper (Semiprecious stone) 12X, Equisetum (Common horsetail) 15X

Inactive Ingredients: Water, Salt, Lactose

PURPOSE

Use: Temporary relief of headache.

KEEP OUT OF REACH OF CHILDREN.

WARNINGS

Warnings: Claims based on traditional homeopathic practice, not accepted medical evidence. Not FDA evaluated. Do not use if allergic to any ingredient. Contains traces of lactose. Consult a doctor before use for serious conditions or if conditions worsen or persist. If pregnant or nursing, consult a doctor before use.

Questions? Call 866.642.2858
Made by Uriel, East Troy, WI 53120
www.urielpharmacy.com